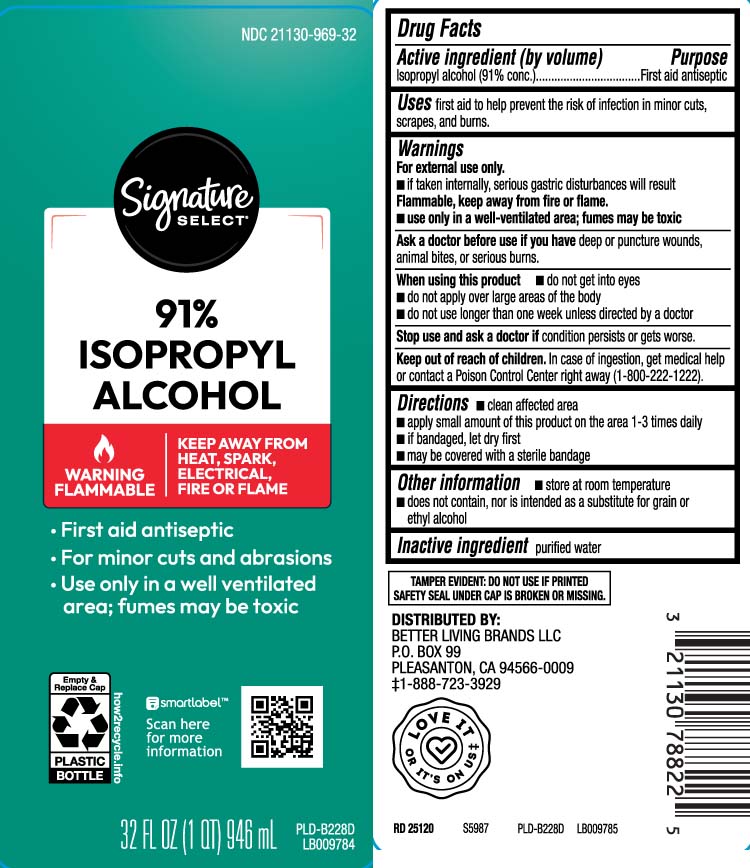 DRUG LABEL: Isopropyl Alcohol
NDC: 21130-969 | Form: LIQUID
Manufacturer: Safeway, Inc.
Category: otc | Type: HUMAN OTC DRUG LABEL
Date: 20250707

ACTIVE INGREDIENTS: ISOPROPYL ALCOHOL 91 mL/100 mL
INACTIVE INGREDIENTS: WATER

Drug Facts

Active ingredient (by volume)

Isopropyl alcohol (91% conc.)

Purpose

First aid antiseptic

Uses

- first aid to help prevent the risk of infection in minor cuts, scrapes and burns.

Warnings

For external use only.

- if taken internally, serious gastic disturbance will result

Flammable, keep away from fire or flame.

- use only in a well-ventilated area; fumes may be toxic

Ask a doctor before use if you have

deep or puncture wounds, animal bites or serious burns.

When using this product

- do not get into eyes
- do not apply over large areas of the body
- do not use longer than one week unless directed by a doctor

Stop use and ask a doctor if

condition persists or gets worse.

Keep out of reach of children.

In case of ingestion, get medical help or contact a Poison Control Center right away (1-800-222-1222).

Directions

- clean affected area
- apply small amount of this product on the area 1-3 times daily
- if bandaged, let dry first
- may be covered with a sterile bandage

Other information

- store at room temperature
- does not contain, nor is intended as a substitute for grain or ethyl alcohol

Inactive ingredient

purified water

Principal Display Panel

91% ISOPROPYL ALCOHOL

WARNING FLAMMABLE | KEEP AWAY FROM HEAT, SPARK, ELECTRICAL, FIRE OR FLAME

- First aid antiseptic
- For minor cuts and abrasions
- Use only in a well ventilated area; fumes may be toxic

TAMPER EVIDENT: DO NOT USE IF PRINTED SAFETY SEAL UNDER CAP IS BROKEN OR MISSING.

DISTRIBUTED BY:

BETTER LIVING BRANDS LLC

P.O. BOX 99

PLEASANTON, CA 94566-0009

Package Label

SIGNATURE SELECT Isopropyl Alcohol 91%